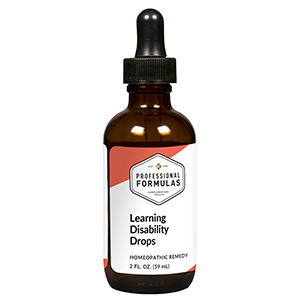 DRUG LABEL: Learning Disability Drops
NDC: 63083-2040 | Form: LIQUID
Manufacturer: Professional Complementary Health Formulas
Category: homeopathic | Type: HUMAN OTC DRUG LABEL
Date: 20190815

ACTIVE INGREDIENTS: CONVALLARIA MAJALIS 6 [hp_X]/59 mL; ORNITHOGALUM UMBELLATUM FLOWERING TOP 6 [hp_X]/59 mL; BOS TAURUS BRAIN 6 [hp_X]/59 mL; SEPIA OFFICINALIS JUICE 8 [hp_X]/59 mL; PHOSPHORUS 10 [hp_X]/59 mL; AMARYLLIS BELLADONNA WHOLE 12 [hp_X]/59 mL; BEEF KIDNEY 30 [hp_X]/59 mL; LYCOPODIUM CLAVATUM SPORE 30 [hp_X]/59 mL
INACTIVE INGREDIENTS: ALCOHOL; WATER

C40

ACTIVE INGREDIENTS

Convallaria majalis 6X
Rescue remedy 6X
Brain 6X, 12X
Sepia 8X
Phosphorus 10X
Belladonna 12X
Kidney 30X
Lycopodium clavatum 30X

QUESTIONS

Professional Formulas

PO Box 2034 Lake Oswego, OR 97035

INDICATIONS

For the temporary relief of reduced memory, perception, comprehension, or focus, difficult expression, or irritability.*

PURPOSE

*Claims based on traditional homeopathic practice, not accepted medical evidence. Not FDA evaluated.

WARNINGS

In case of overdose, get medical help or contact a poison control center right away.

Keep out of the reach of children.

PREGNANCY OR BREAST FEEDING

If pregnant or breastfeeding, ask a healthcare professional before use.

DIRECTIONS

Place drops under tongue 30 minutes before/after meals. Adults and children 12 years and over: Take 10 drops up to 3 times per day. Consult a physician for use in children under 12 years of age.

OTHER INFORMATION

Tamper resistant. If seal is broken, do not use. After opening, close container tightly and store at room temperature away from heat.

INACTIVE INGREDIENTS

10% ethanol, purified water, 8% vegetable glycerin (from soy).

LABEL

Est 1985

Professional Formulas

Complementary Health

Learning Disability Drops

Homeopathic Remedy

2 FL. OZ. (59 mL)